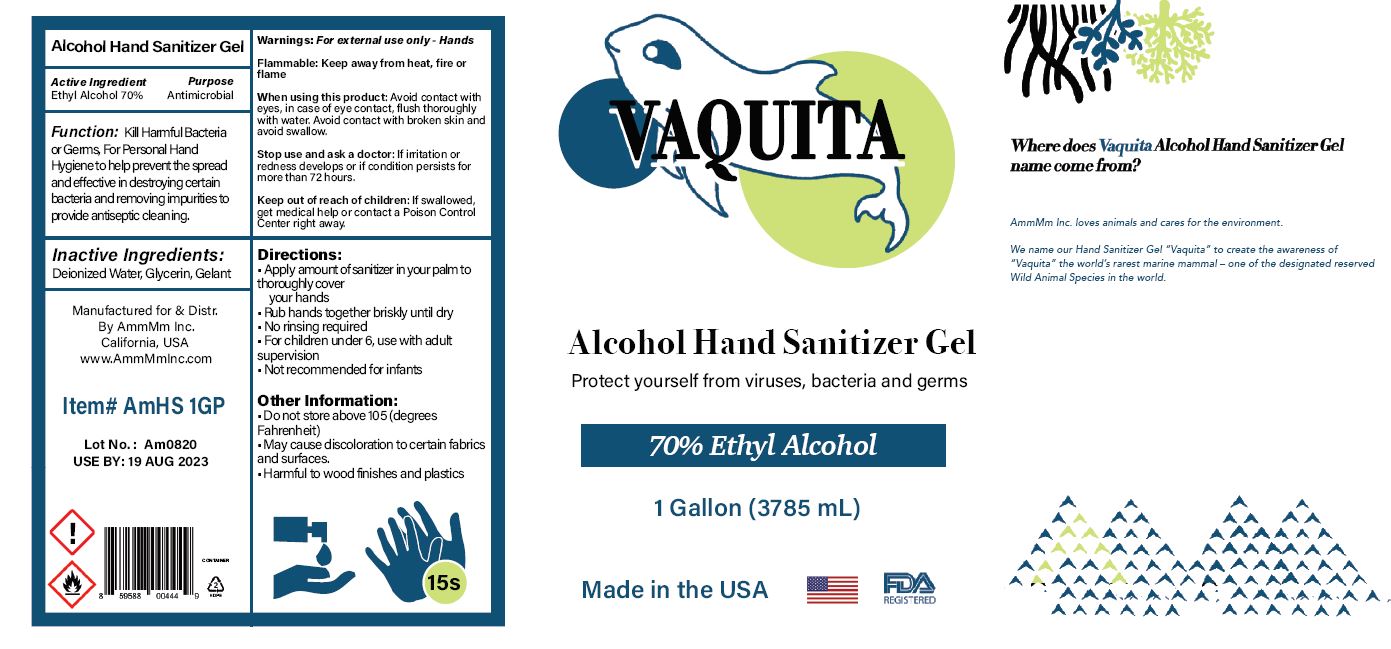 DRUG LABEL: HAND SANITIZER

NDC: 77397-102 | Form: SOLUTION
Manufacturer: AmmMm, Inc.
Category: otc | Type: HUMAN OTC DRUG LABEL
Date: 20220117

ACTIVE INGREDIENTS: ALCOHOL 70 mL/100 mL
INACTIVE INGREDIENTS: WATER; GLYCERIN; CARBOMER HOMOPOLYMER, UNSPECIFIED TYPE; AMINOMETHYLPROPANOL

AmmMm ALCOHOL HAND SANITIZER GEL - 70% Ethyl Alcohol (77397-102)

Active ingredient

Ethyl Alcohol 70%

PURPOSE

ANTIBACTERIAL

FUNCTION:

70% Alcohol Hand Sanitizers, kill 99.9% of the bacteria on hands with 2.5 ml of solution for 15 seconds after application.

Warnings

FOR EXTERNAL USE ONLY - HANDS

FLAMMABLE: KEEP AWAY FROM HEAT, FIRE OR FLAME.

WHEN USING THIS PRODUCT: AVOID CONTACT WITH EYES. IN CASE OF EYE CONTACT, FLUSH WITH THOROUGHLY WATER. AVOID CONTACT WITH BROKEN SKIN AND AVOID SWALLOW.

STOP USE AND ASK A DOCTOR: IF IRRITATION OR REDNESS DEVELOPS OR IF CONDITION PERSISTS FOR MORE THAN 72 HOURS.

Keep out of reach of children. If swallowed, get medical help or contact a Poison Control Center right away.

Directions

- APPLY AMOUNT OF SANITIZER IN YOUR PALM TO THOROUGHLY COVER YOUR HANDS
- RUB HANDS TOGETHER BRISKLY UNTIL DRY
- NO RINSING REQUIRED
- FOR CHILDREN UNDER 6, USE WITH ADULT SUPERVISION
- NOT RECOMMENDED FOR INFANTS

Inactive ingredients

WATER, GLYCERIN, CARBOMER, AMINOMETHYL PROPANOL

OTHER INFORMATION:

- DO NOT STORE ABOVE 105 (DEGREES FAHRENHEIT)
- MAY CAUSE DISCOLORATION TO CERTAIN FABRICS AND SURFACES
- HARMFUL TO WOOD FINISHES AND PLASTICS